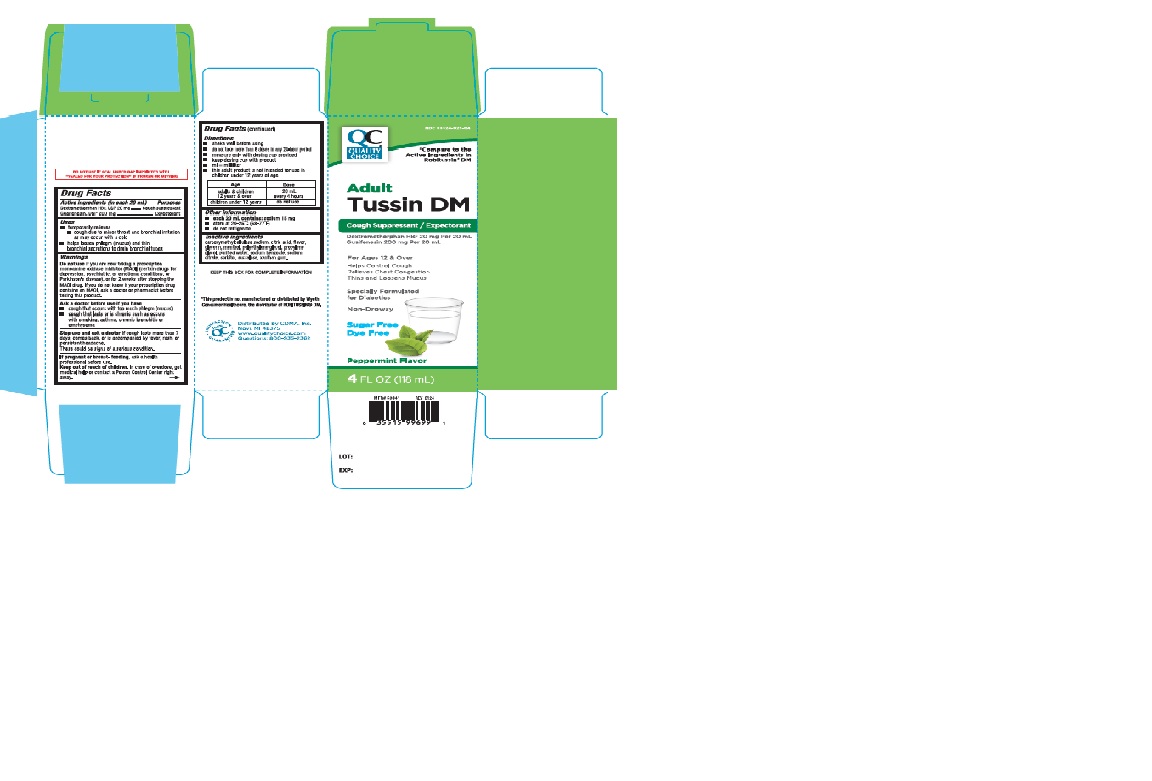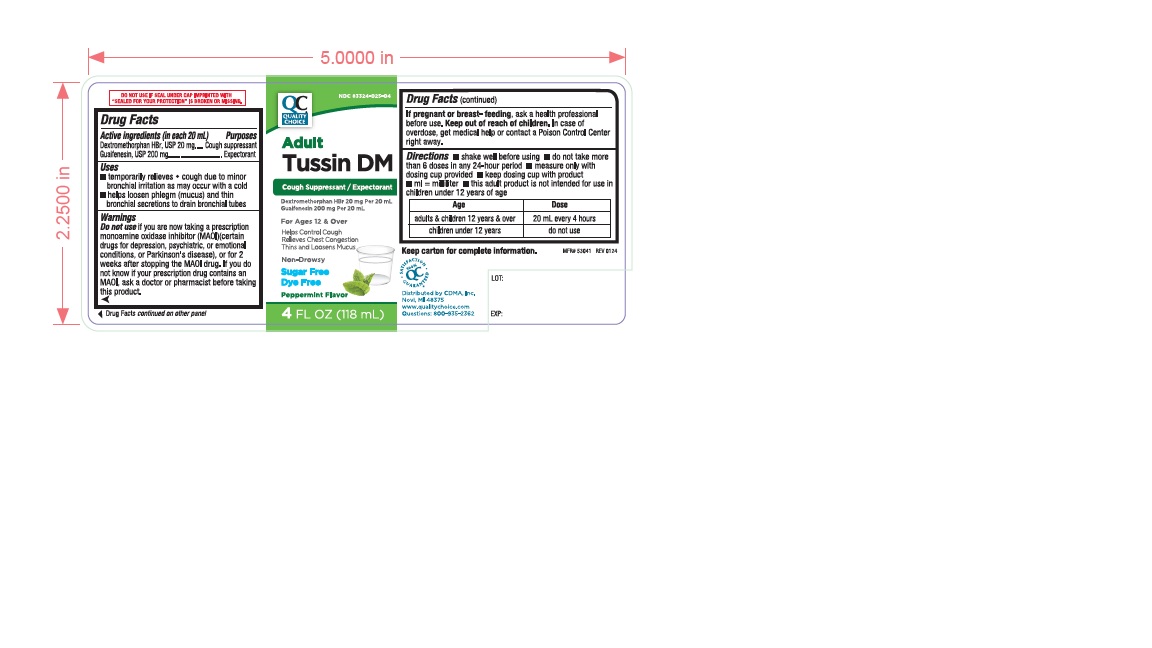 DRUG LABEL: QCH Adult Tussin DM Sugar free 545
NDC: 83324-025 | Form: LIQUID
Manufacturer: Chain Drug Marketing Association Inc.
Category: otc | Type: Human OTC Drug Label
Date: 20240508

ACTIVE INGREDIENTS: DEXTROMETHORPHAN HYDROBROMIDE 20 mg/20 mL; GUAIFENESIN 200 mg/20 mL
INACTIVE INGREDIENTS: CARBOXYMETHYLCELLULOSE SODIUM; ANHYDROUS CITRIC ACID; GLYCERIN; MENTHOL; POLYETHYLENE GLYCOL, UNSPECIFIED; PROPYLENE GLYCOL; WATER; SODIUM BENZOATE; SODIUM CITRATE; SORBITOL; SUCRALOSE; XANTHAN GUM

QCH Adult Tussin DM Sugar Free 545

ACTIVE INGREDIENT(S)

Dextromethorphan HBr, USP 20 mg

Guaifenesin, USP 200 mg

PURPOSE

Cough suppressant

Expectorant

USE(S)

- temporarily relieves
- cough due to minor throat and bronchial irritation as may occur with a cold
- helps loosen phlegm (mucus)and thin bronchial secretions to drain bronchial tubes

WARNINGS

.

DO NOT USE

if you are now taking a prescription monoamine oxidase inhibitor (MAOI) (certain drugs for depression, psychiatric, or emotional conditions, or Parkinson's disease), or for 2 weeks after stopping the MAOI drug. if you do not know if your prescription drug contains an MAOI, ask a doctor or pharmacist before taking this product.

ASK A DOCTOR BEFORE USE IF YOU HAVE

- cough that occurs with too much phlegm (mucus)
- cough that lasts or is chronic such as occurs with smoking, asthma, chronic bronchitis or emphysema

STOP USE AND ASK DOCTOR IF

cough lasts more than 7 days, comes back, or is accompanied by fever, rash, or persistent headache.

These could be signs of a serious condition.

IF PREGNANT OR BREAST-FEEDING,

ask a health professional before use.

KEEP OUT OF REACH OF CHILDREN.

In case of overdose, get medical help or contact a Poison Control Center right away.

DIRECTIONS

- shake well before using
- do not take more than 6 doses in any 24-hour period
- measure only with dosing cup provided
- keep dosing cup with product
- ml=milliliter
- this adult product is not intended for use in children under 12 years of age

Age | Dose
adults & children 12 years & over | 20 mL every 4 Hours
Children under 12 years | do not use

OTHER INFORMATION

- each 20 mL contains: sodium 15 mg
- store at 20-25oC (68-77oF)
- do not refrigerate

INACTIVE INGRADIENTS

carboxymethylcellulose sodium, citric acid, flavor, glycerin, menthol, polyethylene glycol, propylene glycol, purified water , sodium benzoate, sodium citrate, sorbitol, sucralose, xanthan gum.

PRINCIPAL DISPLAY PANEL

NDC 83324-025-04

QUALITY CHOICE

* Compare to the Active Ingredients in Robitussin® DM

Adult Tussin DM

Cough Suppressant/ Expectorant

Dextromethorphan HBr 20 mg per 20 mL

Guaifenesin 200 mg per 20 mL

For Ages 12 & Over

Helps Control Cough

Relieves Chest Congestion

Thins and Loosens Mucus

Specially Formulated for Diabetics

Non-Drowsy

Sugar Free Dye Free

Peppermint Flavor

4 FL OZ (118 mL)